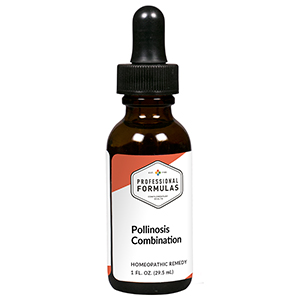 DRUG LABEL: Pollinosis Combination
NDC: 63083-9261 | Form: LIQUID
Manufacturer: Professional Complementary Health Formulas
Category: homeopathic | Type: HUMAN OTC DRUG LABEL
Date: 20190815

ACTIVE INGREDIENTS: SYMPLOCARPUS FOETIDUS ROOT 5 [hp_X]/29.5 mL; ARSENIC TRIOXIDE 6 [hp_X]/29.5 mL; EUPHRASIA STRICTA 6 [hp_X]/29.5 mL; STRYCHNOS IGNATII SEED 6 [hp_X]/29.5 mL; POTASSIUM PHOSPHATE, UNSPECIFIED FORM 6 [hp_X]/29.5 mL; LYCOPODIUM CLAVATUM SPORE 6 [hp_X]/29.5 mL; SANGUINARIA CANADENSIS ROOT 6 [hp_X]/29.5 mL; SULFUR 6 [hp_X]/29.5 mL; HISTAMINE DIHYDROCHLORIDE 9 [hp_X]/29.5 mL
INACTIVE INGREDIENTS: ALCOHOL; WATER

R261

ACTIVE INGREDIENTS

Pothos foetidus 5X
Arsenicum album 6X
Euphrasia officinalis 6X
Ignatia amara 6X
Kali phosphoricum 6X
Lycopodium clavatum 6X
Sanguinaria canadensis 6X
Sulphur 6X
Histaminum hydrochloricum 9X

QUESTIONS

Professional Formulas

PO Box 2034 Lake Oswego, OR 97035

INDICATIONS

For the temporary relief of runny nose, nasal congestion, headache, or itchy and watery eyes due to hay fever or other upper respiratory allergies.*

PURPOSE

*Claims based on traditional homeopathic practice, not accepted medical evidence. Not FDA evaluated.

WARNINGS

If symptoms do not improve or are accompanied by a fever, consult a doctor. Keep out of the reach of children. In case of overdose, get medical help or contact a poison control center right away. If pregnant or breastfeeding, ask a healthcare professional before use.

Keep out of the reach of children.

PREGNANCY OR BREAST FEEDING

If pregnant or breastfeeding, ask a healthcare professional before use.

DIRECTIONS

Place drops under tongue 30 minutes before/after meals. Adults and children 12 years and over: Take 10 drops up to 3 times per day. Consult a physician for use in children under 12 years of age.

OTHER INFORMATION

Tamper resistant. If seal is broken, do not use. After opening, close container tightly and store at room temperature away from heat.

INACTIVE INGREDIENTS

40% ethanol, purified water.

LABEL

Est 1985

Professional Formulas

Complementary Health

Pollinosis Combination

Homeopathic Remedy

1 FL. OZ. (29.5 mL)